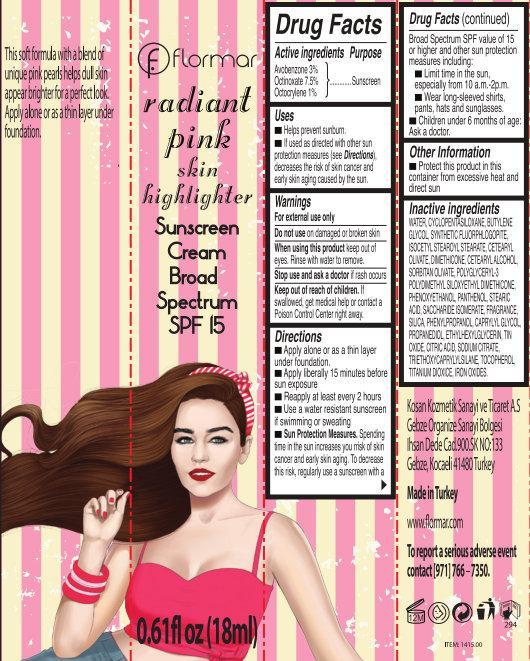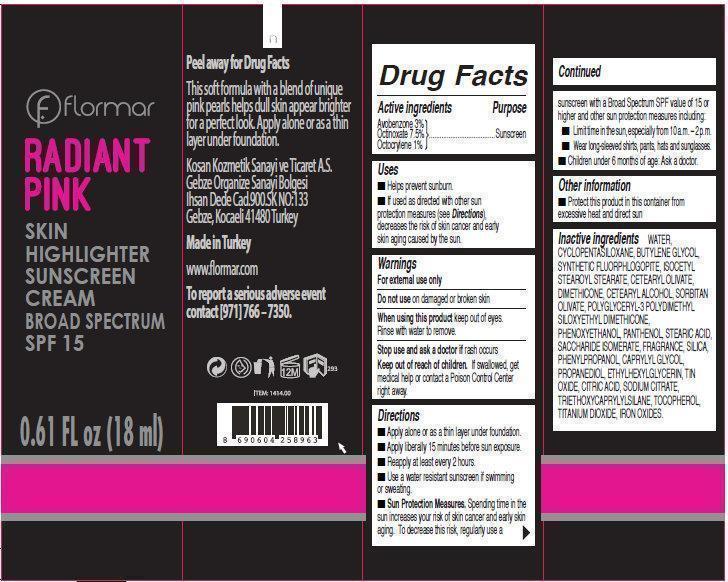 DRUG LABEL: FLORMAR RADIANT PINK SKIN HIGHLIGHTER SUNSCREEN BROAD SPECTRUM SPF 15
NDC: 61722-220 | Form: CREAM
Manufacturer: Kosan Kozmetik Sanayi ve Ticaret A.S.
Category: otc | Type: HUMAN OTC DRUG LABEL
Date: 20191018

ACTIVE INGREDIENTS: AVOBENZONE 30 mg/1 mL; OCTINOXATE 75 mg/1 mL; OCTOCRYLENE 10 mg/1 mL
INACTIVE INGREDIENTS: WATER; CYCLOMETHICONE 5; BUTYLENE GLYCOL; ISOCETYL STEAROYL STEARATE; CETEARYL OLIVATE; DIMETHICONE; CETOSTEARYL ALCOHOL; SORBITAN OLIVATE; PHENOXYETHANOL; PANTHENOL; STEARIC ACID; SACCHARIDE ISOMERATE; SILICON DIOXIDE; PHENYLPROPANOL; CAPRYLYL GLYCOL; PROPANEDIOL; ETHYLHEXYLGLYCERIN; STANNIC OXIDE; CITRIC ACID MONOHYDRATE; SODIUM CITRATE; TRIETHOXYCAPRYLYLSILANE; TOCOPHEROL; TITANIUM DIOXIDE; FERRIC OXIDE RED

FLORMAR RADIANT PINK SKIN HIGHLIGHTER SUNSCREEN BROAD SPECTRUM SPF 15

Active Ingredient

Avobenzone 3%

Octinoxate 7.5%

Octocrylene 1%

Purpose

sunscreen

Uses

- Helps prevent sunburn.
- If used as direct with other sun protection measures (see Directions), decreases the risk of skin cancer and early skin aging caused by the sun.

Warnings

for external use only

Do not use

on damaged or broken skin

When using this product

keep out of eyes. Rinse with water to remove.

Stop use and ask a doctor

if rash occurs

Keep out of reach of children

if swallowed, get medical help or contact a Poison Control Center right away.

Directions

- Apply alone or as a thin layer under foundation.
- Apply liberally 15 minutes before sun exposure.
- Reapply at least every 2 hours.
- Use a water resistant sunscreen if swimming or sweating.
- Sun Protection Measures. Spending time in the sun increases your risk of skin cancer and early skin aging. To decrease this risk, regularly use a sunscreen with a Bord Spectrum SPF value of 15 or higher and other sun protection measures including:
-
  - Limit time in the sun, especially from 10 a.m.-2 p.m.
  - Wear long-sleeved shirts, pants, hats and sunglasses.
- Children under 6 months of age: Ask a doctor.

Other information

- Protect the product in this container from excessive heat and direct sun

Inactive ingredients

WATER,CYCLOPENTASILOXANE, BUTYLENE GLYCOL, SYNTHETIC FLUORPHLOGOPITE, ISOCETYL STEAROYL STEARATE, CETEARYL OLIVATE,
DIMETHICONE, CETEARYL ALCOHOL, SORBITAN OLIVATE, POLYGLYCERYL-3 POLYDIMETHYL SILOXYETHYL DIMETHICONE, PHENOXYETHANOL, PANTHENOL, STEARIC ACID, SACCHARIDE ISOMERATE, FRAGRANCE, SILICA, PHENYLPROPANOL, CAPRYLYL GLYCOL, PROPANEDIOL, ETHYLHEXYLGLYCERIN, TIN OXIDE, CITRIC ACID, SODIUM CITRATE, TRIETHOXYCAPRYLYLSILANE, TOCOPHEROL, TITANIUM DIOXIDE, IRON OXIDES.

Peel away for Drug Facts

This soft formula with a blend of unique pink pearls helps dull skin appear brighter for a perfect look. Apply alone or as a thin layer under foundation. Kosan Kozmetik Sanayi ve Ticaret A.S. Gebze Organize Sanayi Bolgesi Ihsan Dede Cad. 900.SK No. 133 Gebze, Kocaeli 41480 Turkey Made in Turkey www.flormar.com To report a serious adverse event contact [971] 766-7350

PACKAGE LABEL

Flormar RADIANT PINK SKIN HIGHLIGHTER SUNSCREEN CREAM BROAD SPECTRUM SPF 15 0.61 FL oz (18 ml)